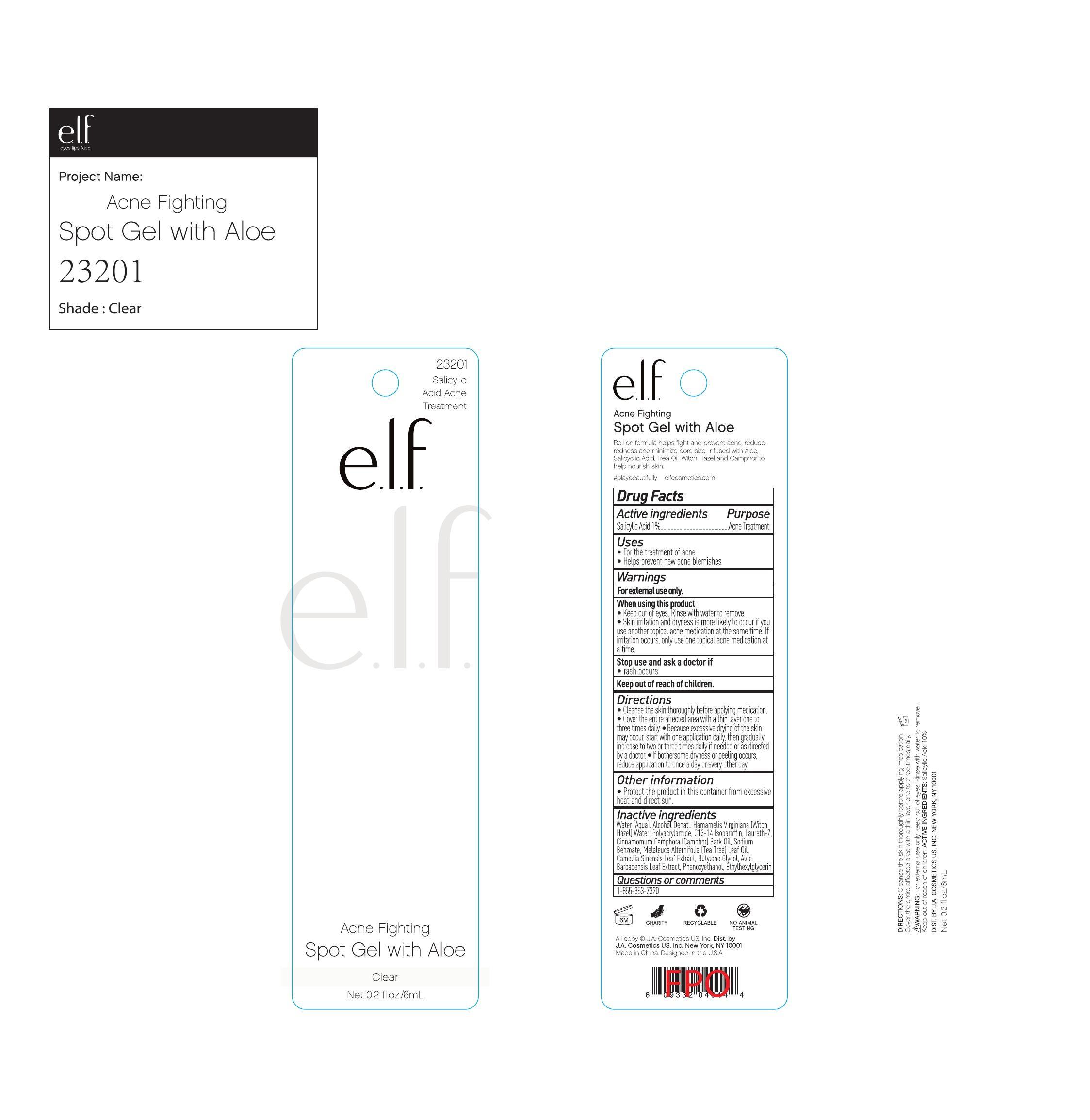 DRUG LABEL: ELF ACNE Fighting Spot Gel with Aloe Clear
NDC: 76354-616 | Form: GEL
Manufacturer: e.l.f. Cosmetics, Inc
Category: otc | Type: HUMAN OTC DRUG LABEL
Date: 20241106

ACTIVE INGREDIENTS: SALICYLIC ACID 1 g/100 mL
INACTIVE INGREDIENTS: POLYACRYLAMIDE (10000 MW); WATER; ALCOHOL; CAMPHOR OIL; C13-14 ISOPARAFFIN; LAURETH-7; SODIUM BENZOATE; CAMELLIA SINENSIS WHOLE; PHENOXYETHANOL; BUTYLENE GLYCOL; ETHYLHEXYLGLYCERIN; TEA TREE OIL; ALOE VERA LEAF; WITCH HAZEL

Drug Fact

Active Ingredient:

Salicylic Acid 1.0 %

Purpose:

Acne Treatment

Uses:

For the treatment of acne

Helps prevent new acne blemishes

Warning:

For external use only

When Using This Product:

Keep out of eyes, rinse with water to remove.

Skin irrittion and dryness is more likely to occur if you use another topical acne medications at the same time. If irritation occurs, only use one medication at a time.

Stop use and ask a doctor If

rash occurs

Keep Out of Reach of Children

Directions:

Cleanse the skin thoroughly before applying medication. Cover the entire affected area with a thin layer one to three times daily. Because excessive drying of skin may occur, start with one application daily, then gradually increase to two or three times daily if needed or as directed by a doctor. If bothersome dryness or peeling occurs, reduce application to once a day or every other day.

Other Information:

Protect the product in this container from exessive heat and direct sun

Inactive Ingredient:

Water, Alcohol Denat, Hamamelis Birginiana (Witch Hazel), Polyacrylamide, C13-14 Isoparaffin, Laureth-7, Cinnamomum Camphora (Camphor) Bark oil, Sodium Benzoate, Melaleuca Alternafolia (Tea Tree) Leaf Oil, Camellia Sinensis Leaf Extract, Butylene Glycol, Aloe Barbadensis Leaf Extract, Phenoxyethanol, Ethylhexylglycerin